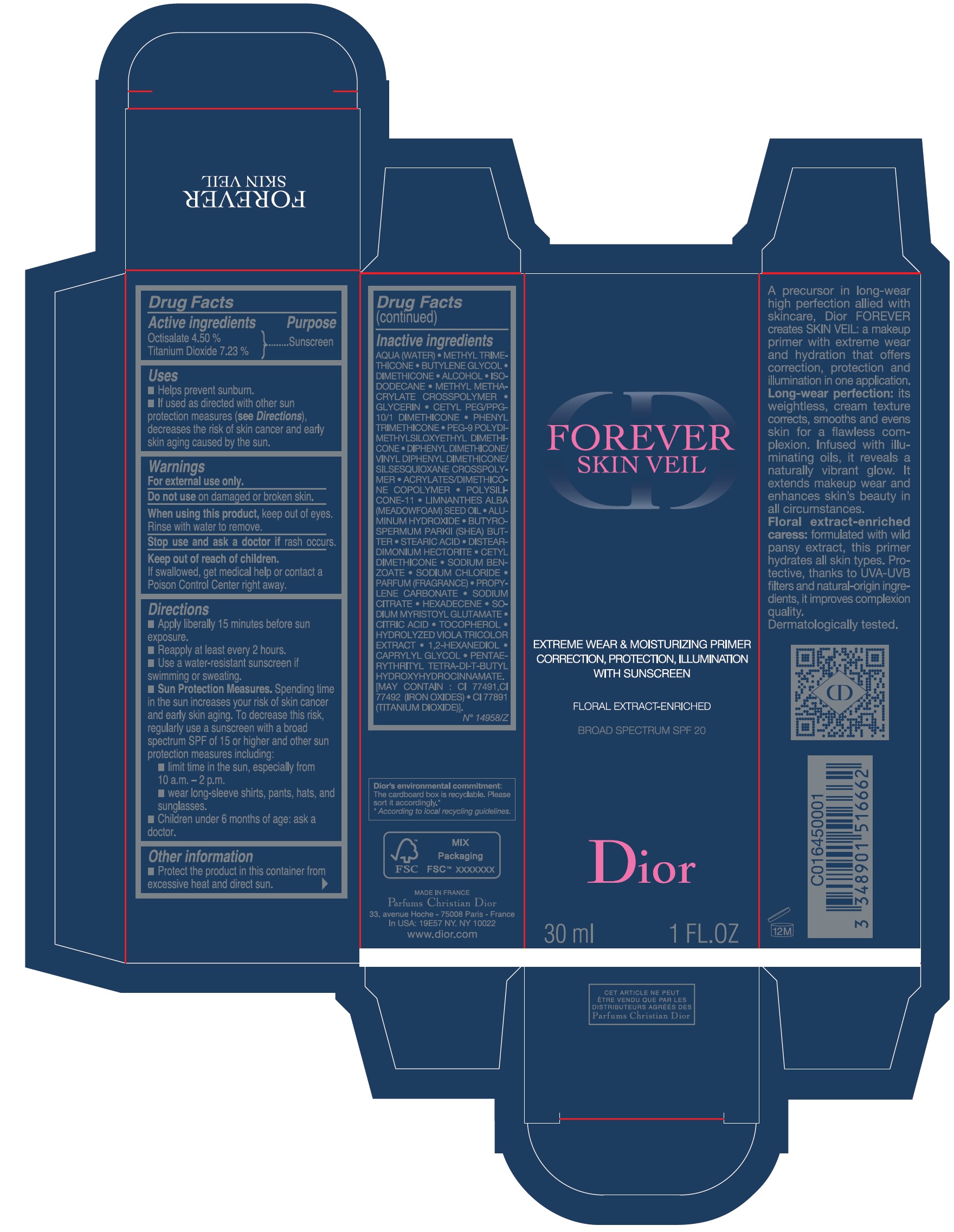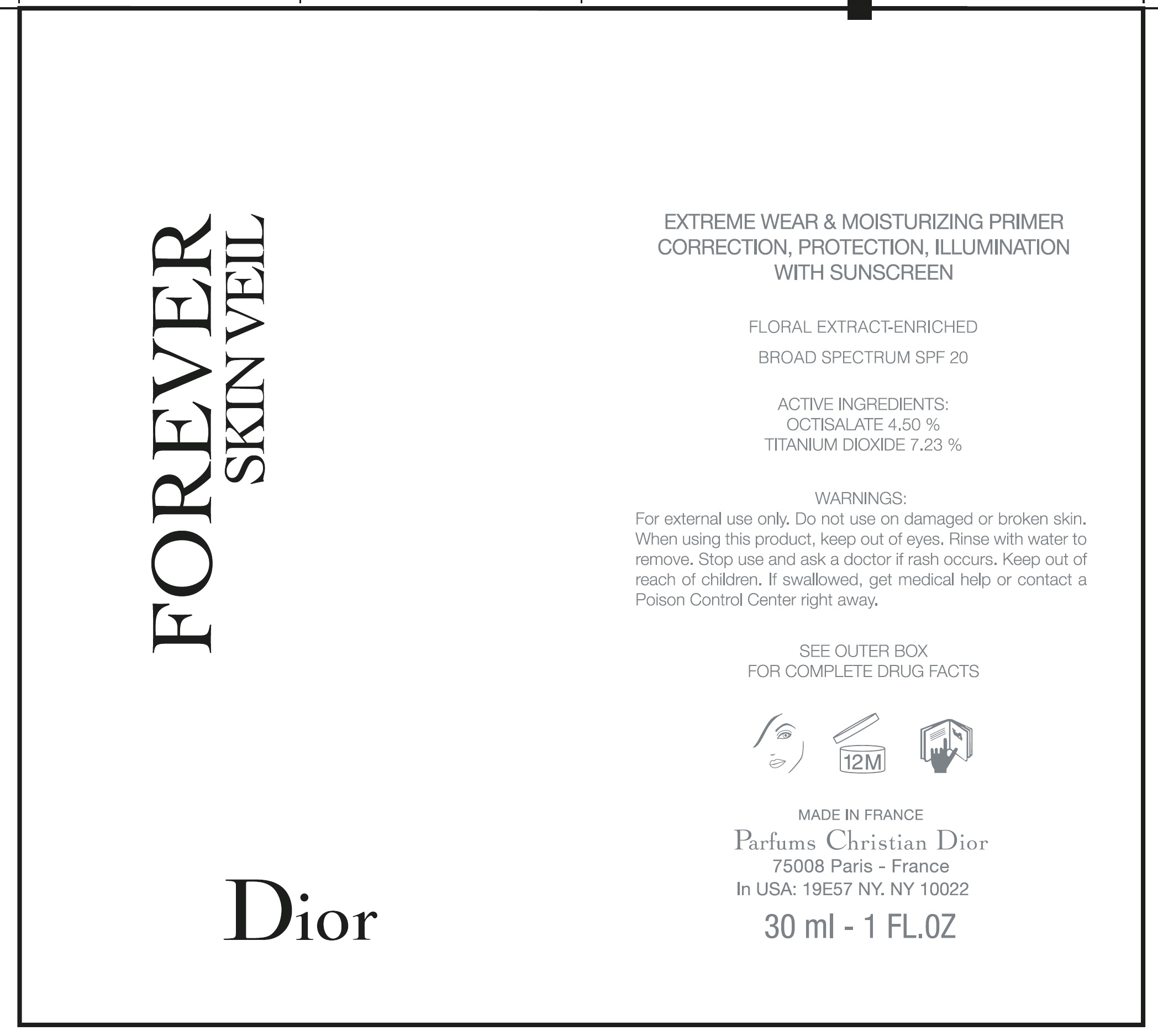 DRUG LABEL: FOREVER SKIN VEIL Extreme Wear and Moisturizing Primer Correction, Protection, Illumination With Sunscreen Floral Extract-Enriched Broad Spectrum SPF20
NDC: 61957-2740 | Form: EMULSION
Manufacturer: Parfums Christian Dior
Category: otc | Type: HUMAN OTC DRUG LABEL
Date: 20231103

ACTIVE INGREDIENTS: OCTISALATE 45 mg/1 mL; TITANIUM DIOXIDE 72.3 mg/1 mL
INACTIVE INGREDIENTS: WATER; METHYL TRIMETHICONE; BUTYLENE GLYCOL; ALCOHOL; ISODODECANE; METHYL METHACRYLATE/GLYCOL DIMETHACRYLATE CROSSPOLYMER; GLYCERIN; CETYL PEG/PPG-10/1 DIMETHICONE (HLB 2); PHENYL TRIMETHICONE; PEG-9 POLYDIMETHYLSILOXYETHYL DIMETHICONE; DIPHENYL DIMETHICONE (100 CST); ACRYLIC ACID; DIMETHICONE/VINYL DIMETHICONE CROSSPOLYMER (SOFT PARTICLE); MEADOWFOAM SEED OIL; ALUMINUM HYDROXIDE; SHEA BUTTER; STEARIC ACID; DISTEARDIMONIUM HECTORITE; SODIUM BENZOATE; SODIUM CHLORIDE; PROPYLENE CARBONATE; SODIUM CITRATE; HEXADECENE (MIXED ISOMERS); SODIUM MYRISTOYL GLUTAMATE; CITRIC ACID MONOHYDRATE; TOCOPHEROL; 1,2-HEXANEDIOL; CAPRYLYL GLYCOL; PENTAERYTHRITOL TETRAKIS(3-(3,5-DI-TERT-BUTYL-4-HYDROXYPHENYL)PROPIONATE); FERRIC OXIDE RED; FERRIC OXIDE YELLOW

FOREVER SKIN VEIL Extreme Wear & Moisturizing Primer Correction, Protection, Illumination With Sunscreen Floral Extract-Enriched Broad Spectrum SPF20

Active ingredients

Octisalate 4.50% Titanium Dioxide 7.23%

Purpose

Sunscreen

Uses

- Helps prevent sunburn.
- If used as directed with other sun protection measures (), decreases the risk of skin cancer and early skin aging caused by the sun. see Directions

Warnings

For external use only.

Do not use

on damaged or broken skin.

When using this product,

keep out of eyes. Rinse with water to remove.

Stop use and ask a doctor if

rash occurs.

Keep out of reach of children.

If swallowed, get medical help or contact a Poison Control Center right away.

Directions

- Apply liberally 15 minutes before sun exposure.
- Reapply at least every 2 hours.
- Use water-resistant sunscreen if swimming or sweating.
- Spending time in the sun increases your risk of skin cancer and early skin aging. To decease this risk, regularly use sunscreen with a broad spectrum SPF of 15 or higher and other sun protection measures including: Sun Protection Measures.
- limit time in the sun, especially from 10 a.m.-2 p.m.
- wear long-sleeved shirts, pants, hats, and sunglasses.
- Children under 6 months of age: ask a doctor.

Other information

- Protect the product in this container from excessive heat and direct sun.

Inactive ingredients

AQUA (WATER), METHYL TRIMETHICONE, BUTYLENE GLYCOL, ALCOHOL, ISODODECANE, METHYL ETHACRYLATECROSPOLYMER,GLYCERIN, CETYL PEG/PPG-10/1 DIMETHICONE , PHENYL TRIMETHICONE, PEG-9 POLYDIMETHYLILOXY DIMETHICONE, DIPHENYL DIMETHICONE/VINYL DIPHENYL DIMETHICONE/SILSESQUIOXANE CROSPOLYMER, ACRYLATE/DIMETHICONE COPOLYMER, POLYSILICONE-11, LIMANANTHES ALBA(MEADOWFOAM)SEED OIL, ALUMINUM HYDROXIDE, BUTYROSPERMUM PARKII (SHEA) BUTTER, STEARIC ACID, DISTEARDIMONIUM HECTORITE, CETYLDIMETHICONE, SODIUM BENZOATE, SODIUM CHLORIDE, PARFUME (FRAGRANCE), PROPYLENE CARBONATE, SODIUM CITRATE, HEXADECENE, SODIUM MYRITOYL GLUTAMATE, CITRIC ACID, TOCOPHEROL, HYDROLYZED VIOLA TRICOLOR EXTRACT, 1,2-HEXANEDIOL, CAPRYLYL GLYCOL, PENTATERYTHRITYL TETRA-DI-T-BUTYL HYDROXYHYDROCINNAMATE.

[MAY CONTAIN: CI 77491, CI 77492 (IRON OXIDES), CI 77891 (TITANIUM DIOXIDE)]. N 14958/Z